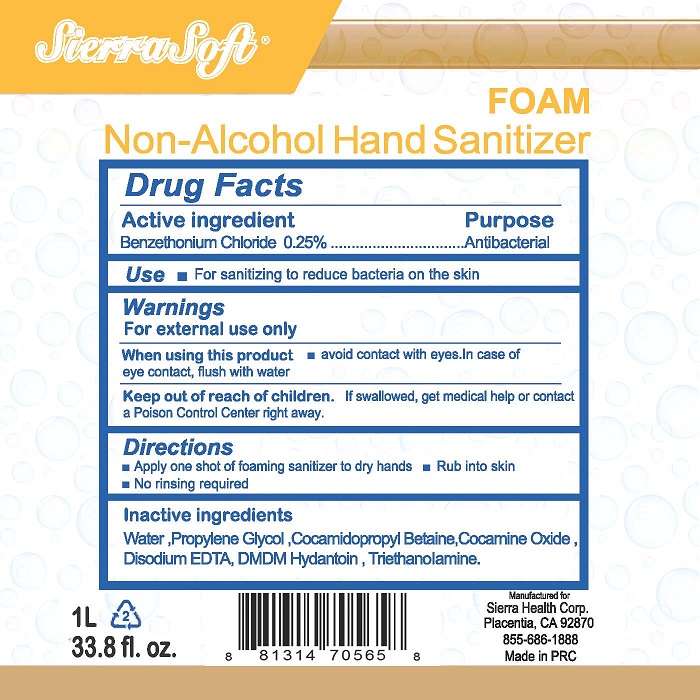 DRUG LABEL: Sierra Soft Non-Alcohol Hand Sanitizer Foam
NDC: 70415-104 | Form: LIQUID
Manufacturer: CWGC LA Inc.
Category: otc | Type: HUMAN OTC DRUG LABEL
Date: 20230921

ACTIVE INGREDIENTS: BENZETHONIUM CHLORIDE 2.5 g/1 L
INACTIVE INGREDIENTS: WATER; PROPYLENE GLYCOL; COCAMIDOPROPYL BETAINE; COCAMINE OXIDE; EDETATE DISODIUM; DMDM HYDANTOIN; TROLAMINE

CWGC (as PLD) - Sierra Soft Non-Alcohol Hand Sanitizer Foam (70415-104)

Active ingredient

BENZETHONIUM CHLORIDE 0.25%

Purpose

Antibacterial

Uses

- For sanitizing to reduce bacteria on the skin.

Warnings

For external use only

When using this product

- avoid contact with eyes. In case of eye contact, flush with water

Keep out of reach of children.

If swallowed, get medical help or contact a Poison Control Center right away.

Directions

- Apply one shot of foaming sanitizer to dry hands
- Rub into skin
- No rinsing required

Inactive ingredients

WATER, PROPYLENE GLYCOL, COCAMIDOPROPYL BETAINE, COCAMINE OXIDE, DISODIUM EDTA, DMDM HYDANTOIN, TRIETHANOLAMINE.